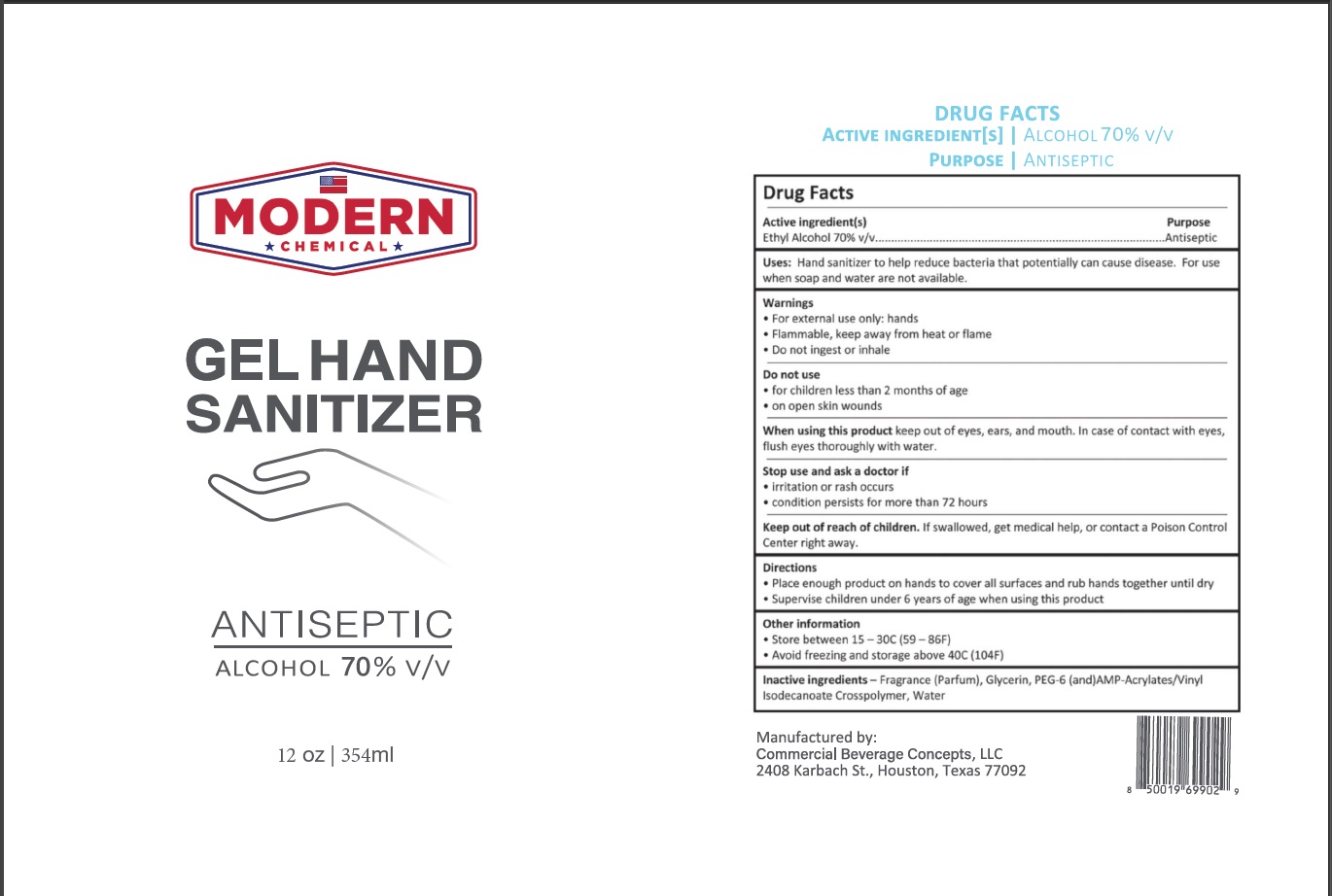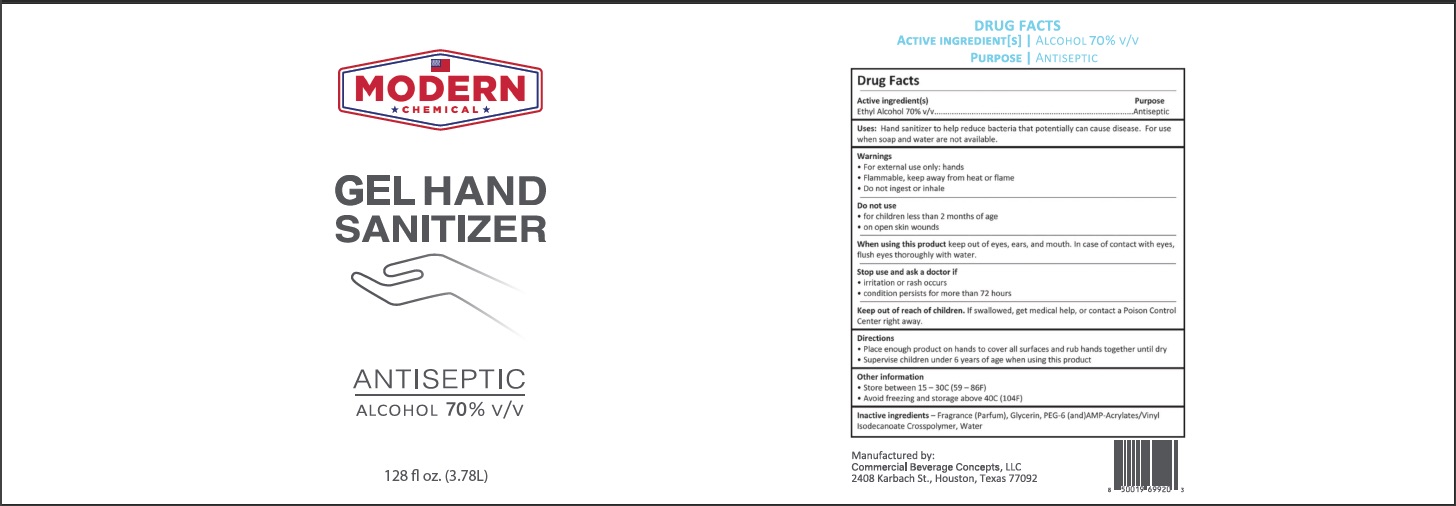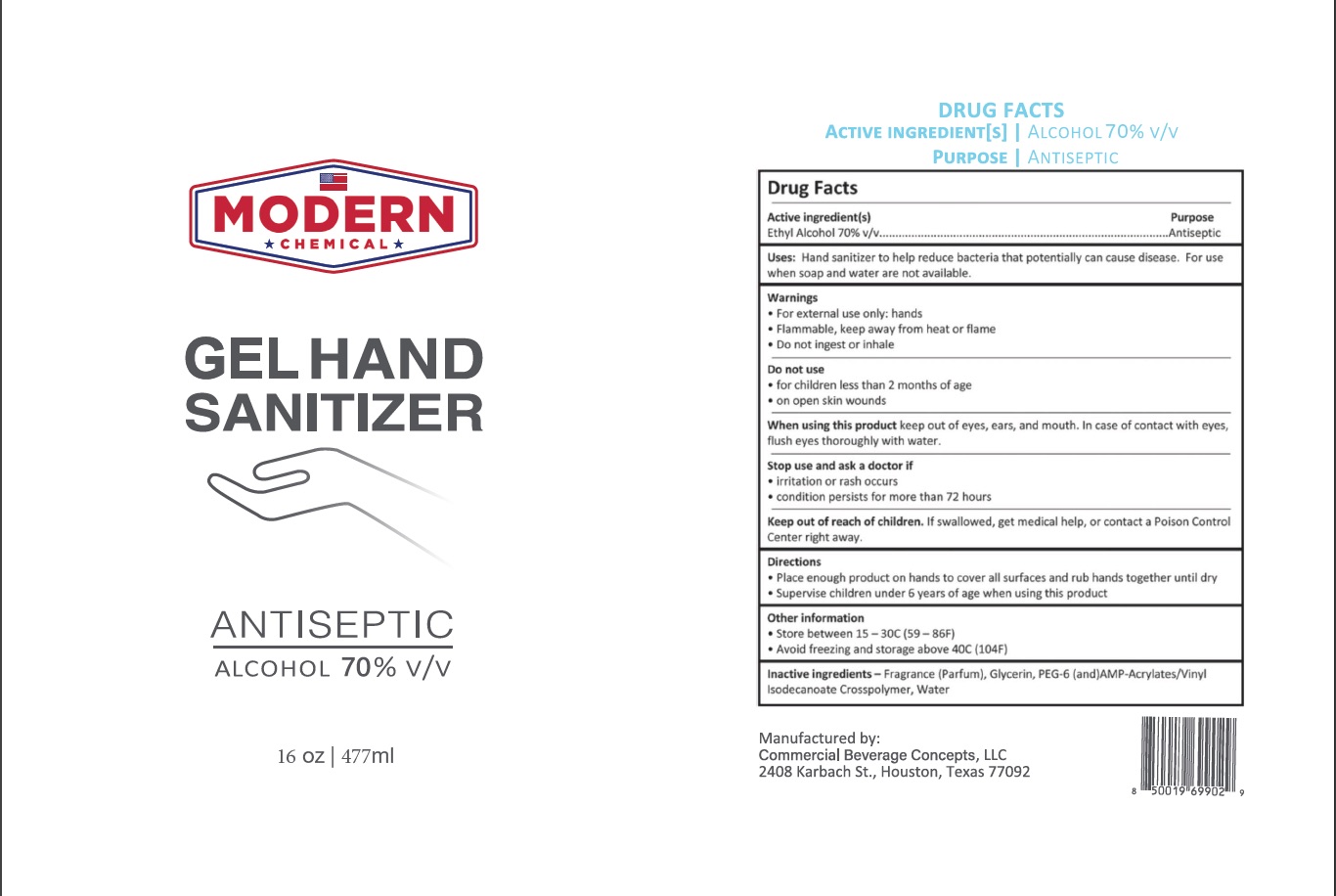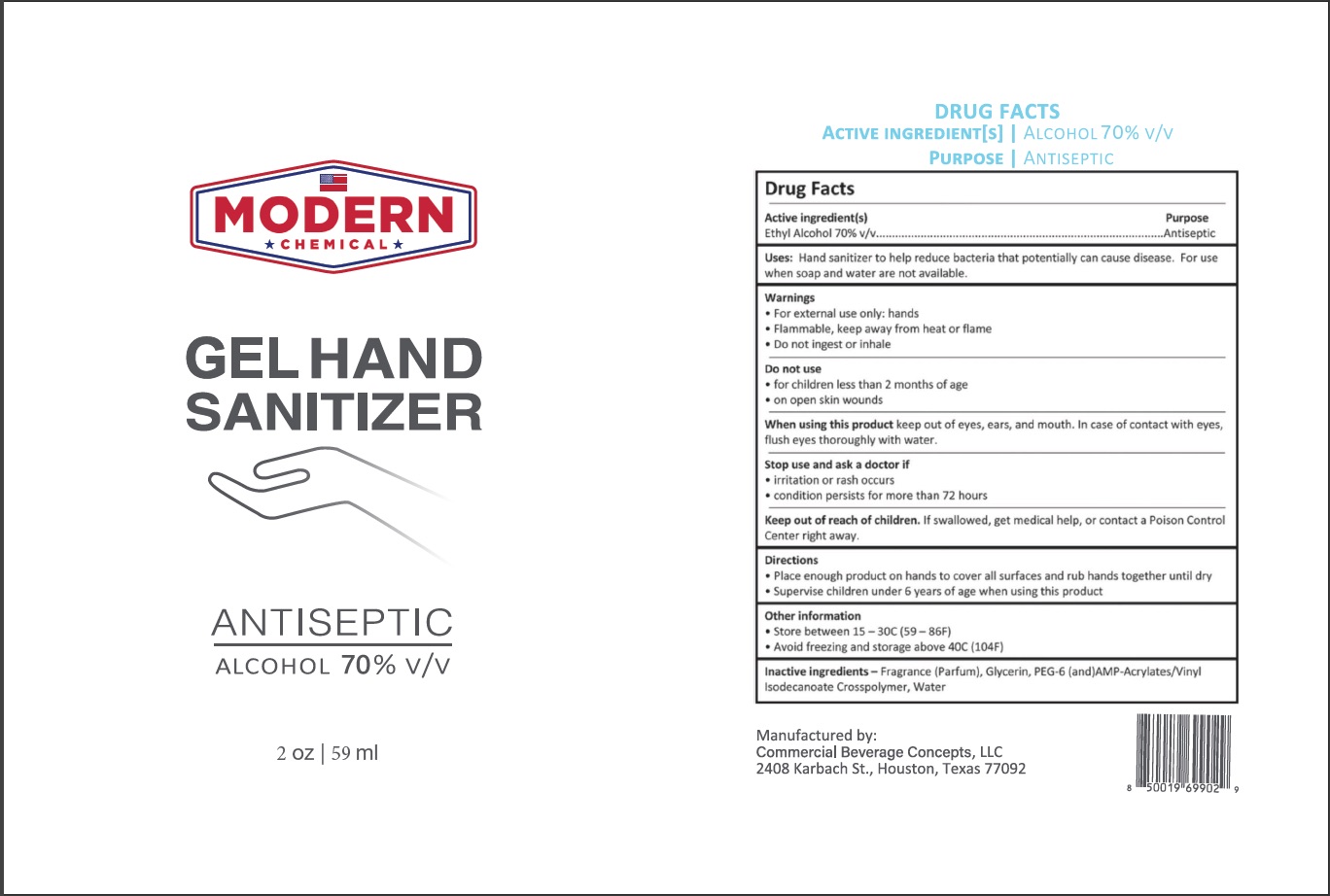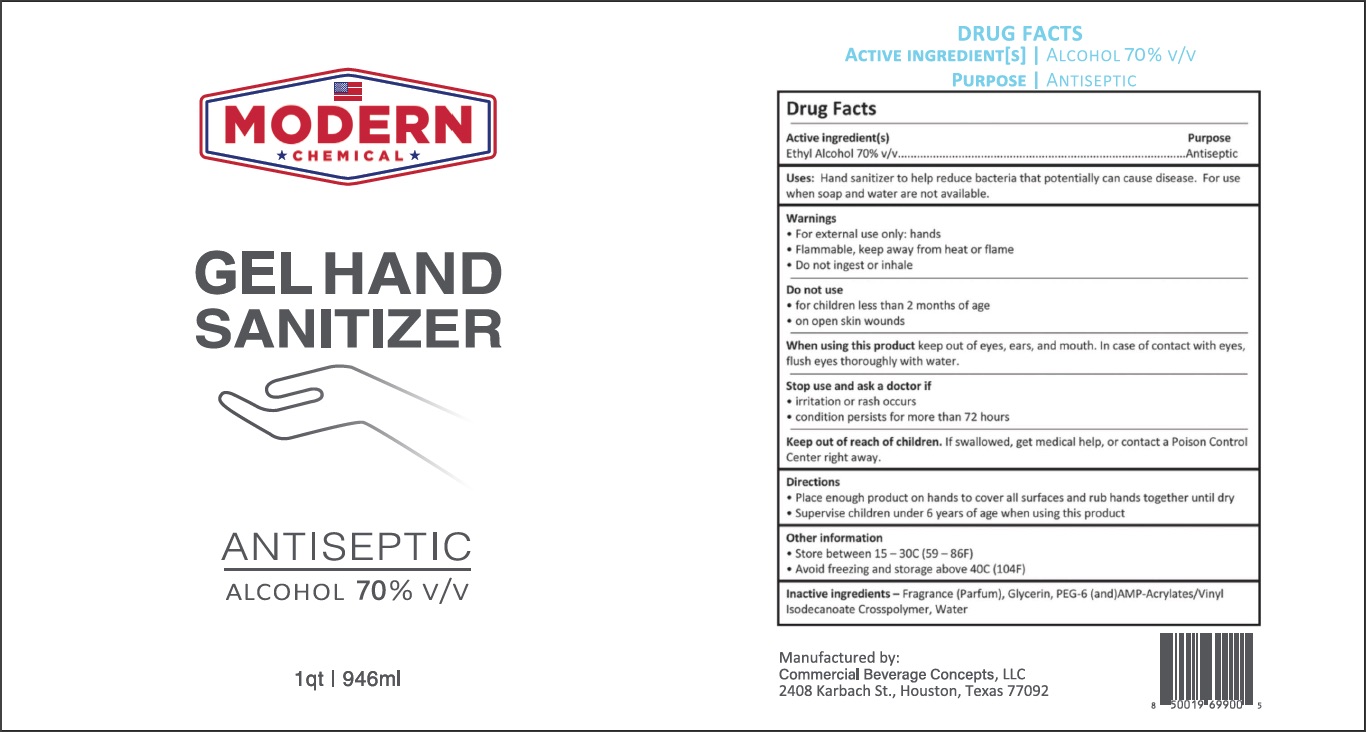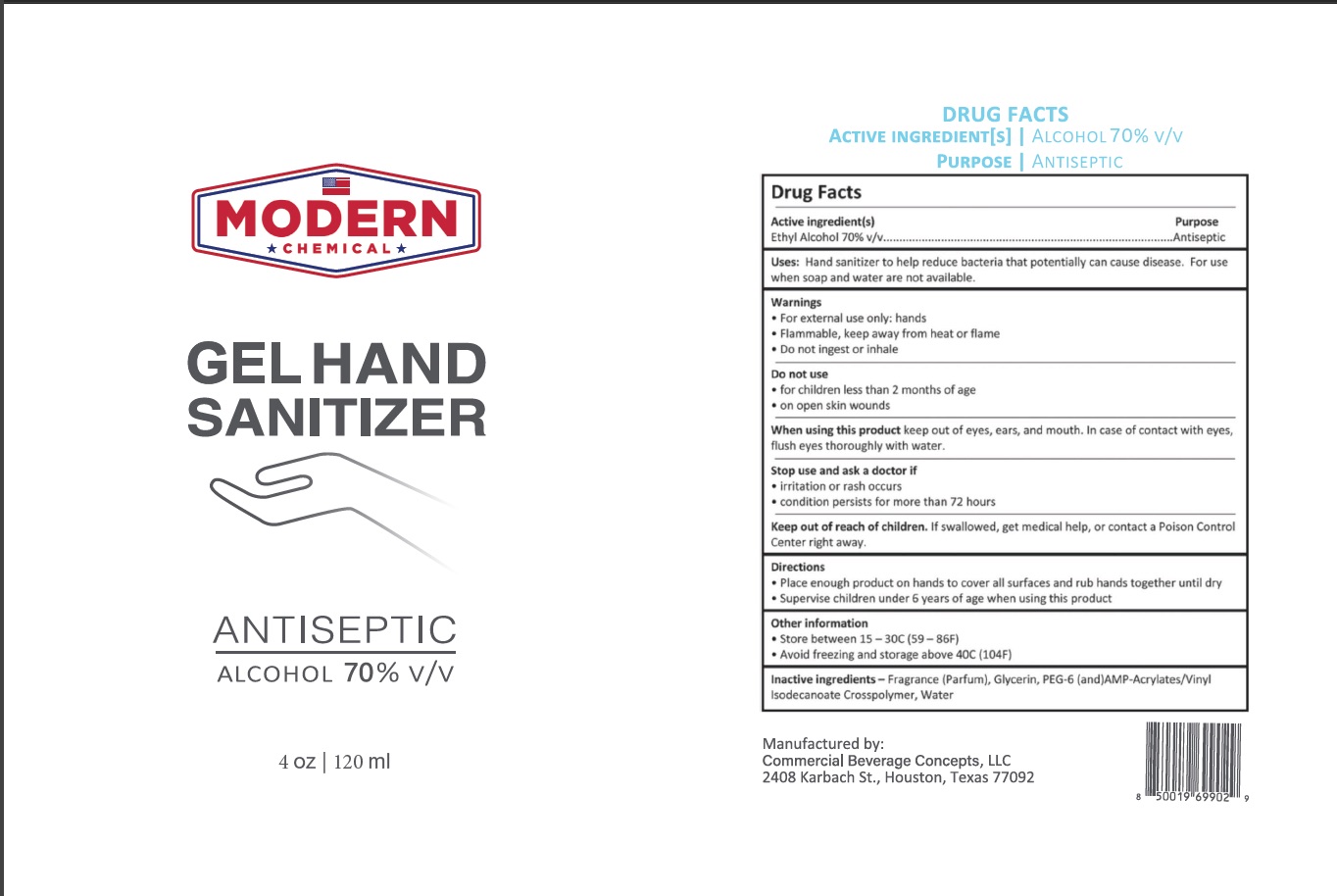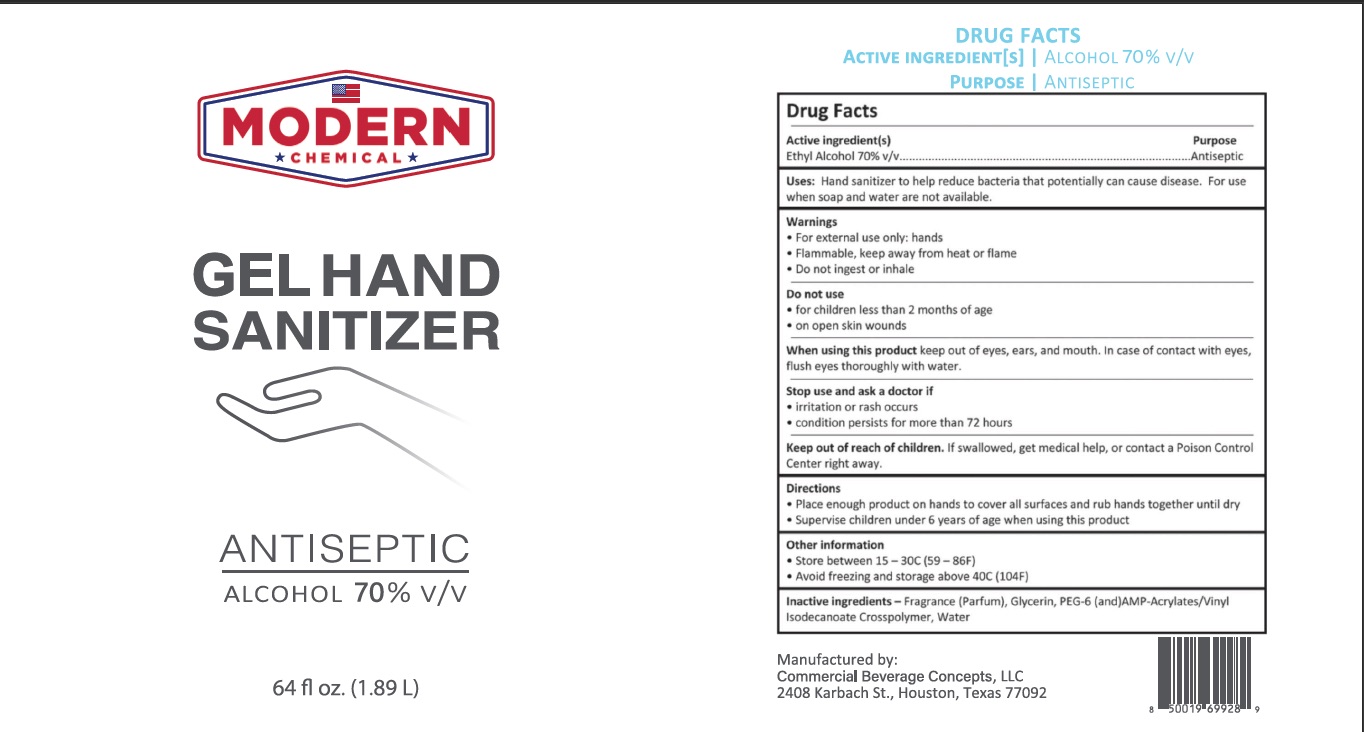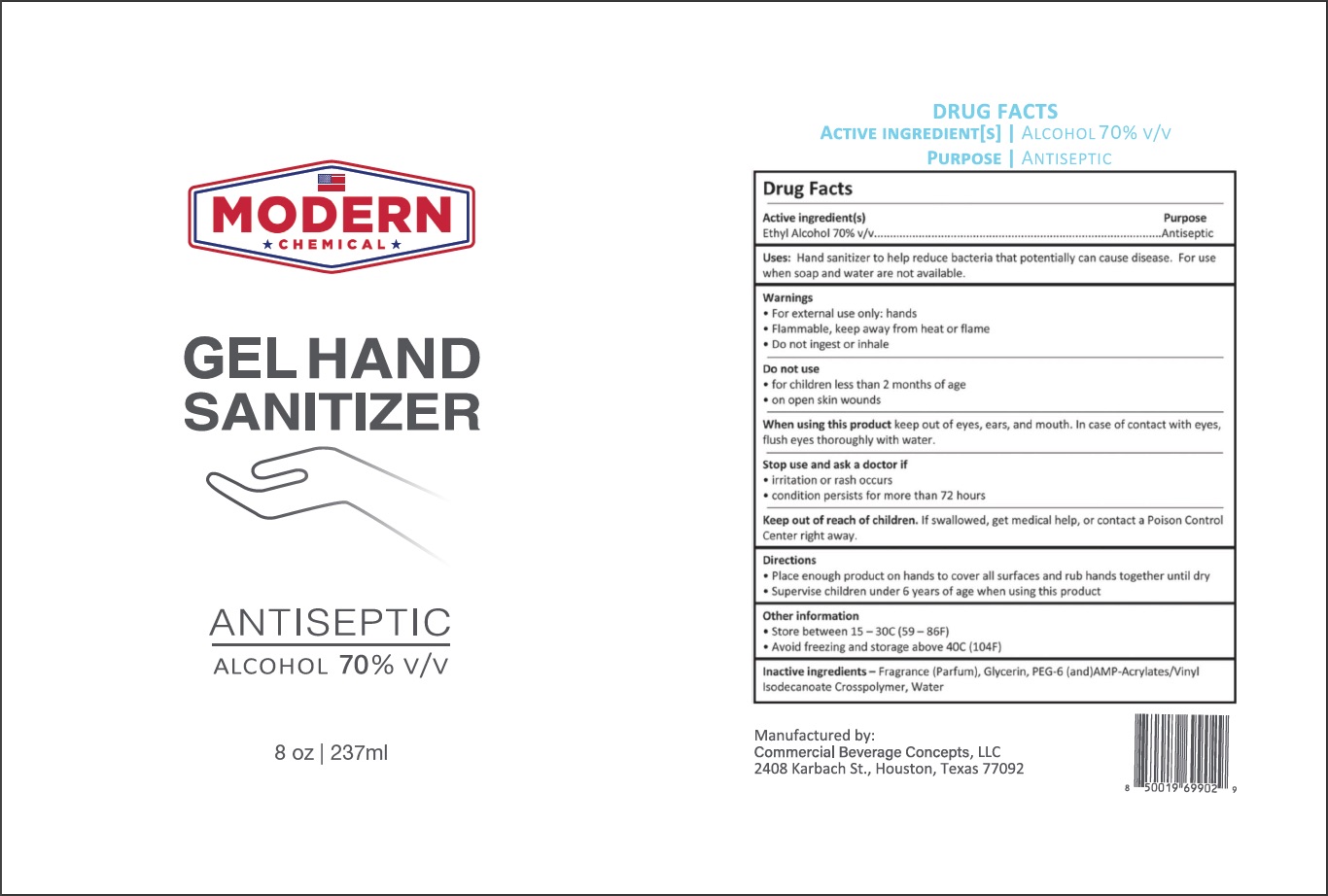 DRUG LABEL: Hand Sanitizer
NDC: 75594-006 | Form: GEL
Manufacturer: Commercial Beverage Concepts, LLC
Category: otc | Type: HUMAN OTC DRUG LABEL
Date: 20200812

ACTIVE INGREDIENTS: ALCOHOL 70 L/100 L
INACTIVE INGREDIENTS: GLYCERIN; RAPIDGEL EZ1; WATER

Active Ingredient(s)

Ethyl Alcohol 70% v/v. Purpose: Antiseptic

Purpose

Antiseptic

Use

Hand Sanitizer to help reduce bacteria that potentially can cause disease. For use when soap and water are not available.

Warnings

For external use only. Flammable. Keep away from heat or flame. Do not ingest or inhale.

Do not use

- for children less than 2 months of age
- on open skin wounds

When using this product keep out of eyes, ears, and mouth. In case of contact with eyes, rinse eyes thoroughly with water.

Stop use and ask a doctor if irritation or rash occurs. Condition persists for more than 72 hours.

Keep out of reach of children. If swallowed, get medical help or contact a Poison Control Center right away.

Directions

- Place enough product on hands to cover all surfaces. Rub hands together until dry.
- Supervise children under 6 years of age when using this product to avoid swallowing.

Other information

- Store between 15-30C (59-86F)
- Avoid freezing and excessive heat above 40C (104F)

Inactive ingredients

Fragrance (parfum), Glycerin, PEG-6 (and) AMP-Acrylates/Vinyl Isodecanoete Crosspolymer, Water

Package Label - Principal Display Panel

3.78L, NDC: 75594-006-08

.059L, NDC: 75594-006-01

.12L, NDC: 75594-006-02

.354L, NDC: 75594-006-04

.237L, NDC: 75594-006-03

.477L, NDC: 75594-006-05

.946L, NDC: 75594-006-06

1.89L, NDC: 75594-006-07